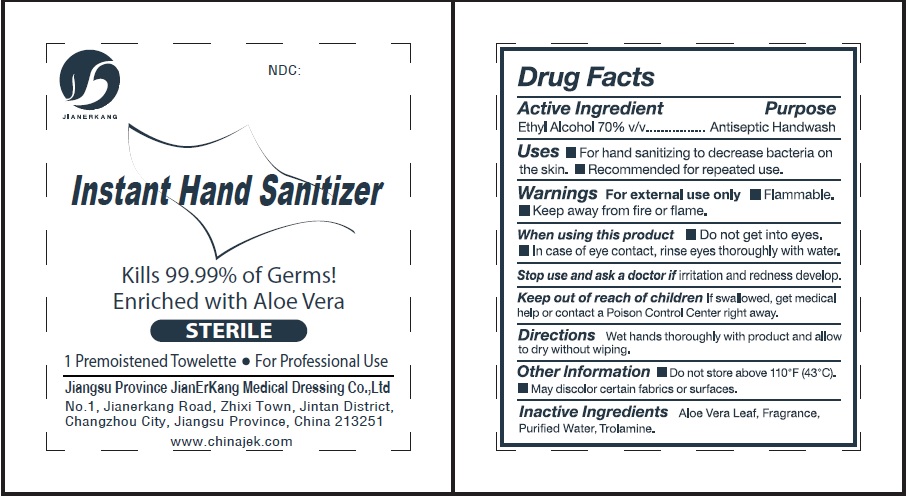 DRUG LABEL: Instant Hand Sanitizer STERILE 70 Ethyl Alcohol
NDC: 34645-0007 | Form: CLOTH
Manufacturer: Jianerkang Medical Co., Ltd
Category: otc | Type: HUMAN OTC DRUG LABEL
Date: 20231023

ACTIVE INGREDIENTS: ALCOHOL 0.7 mL/1 mL
INACTIVE INGREDIENTS: ALOE VERA LEAF; WATER; TROLAMINE

Instant Hand Sanitizer STERILE, 70% Ethyl Alcohol

Active Ingredient

Ethyl Alohol 70% v/v

Purpose

Antiseptic Handwash

Uses

- For hand sanitizing to decrease bacteria on the skin.
- Recommended for repeated use.

Warnings

- For external use only
- Flammable.
- Keep away from fire or flame.

When using this product

- Do not get into eyes.
- In case of eye contact, rinse eyes thoroughly with water.

Stop use and ask a doctor if

irritation and redness develops.

Keep out of reach of children

If swallowed, get medical help or contact a Poison Control Center right away.

Directions

Wet hands thoroughly with product and allow to dry without wiping.

Other Information

- Do not store above 110°F (43°C).
- May discolor certain fabrics or surfaces.

Inactive Ingredients

Aloe Vera Leaf, Fragrance, Purified Water, Trolamine.